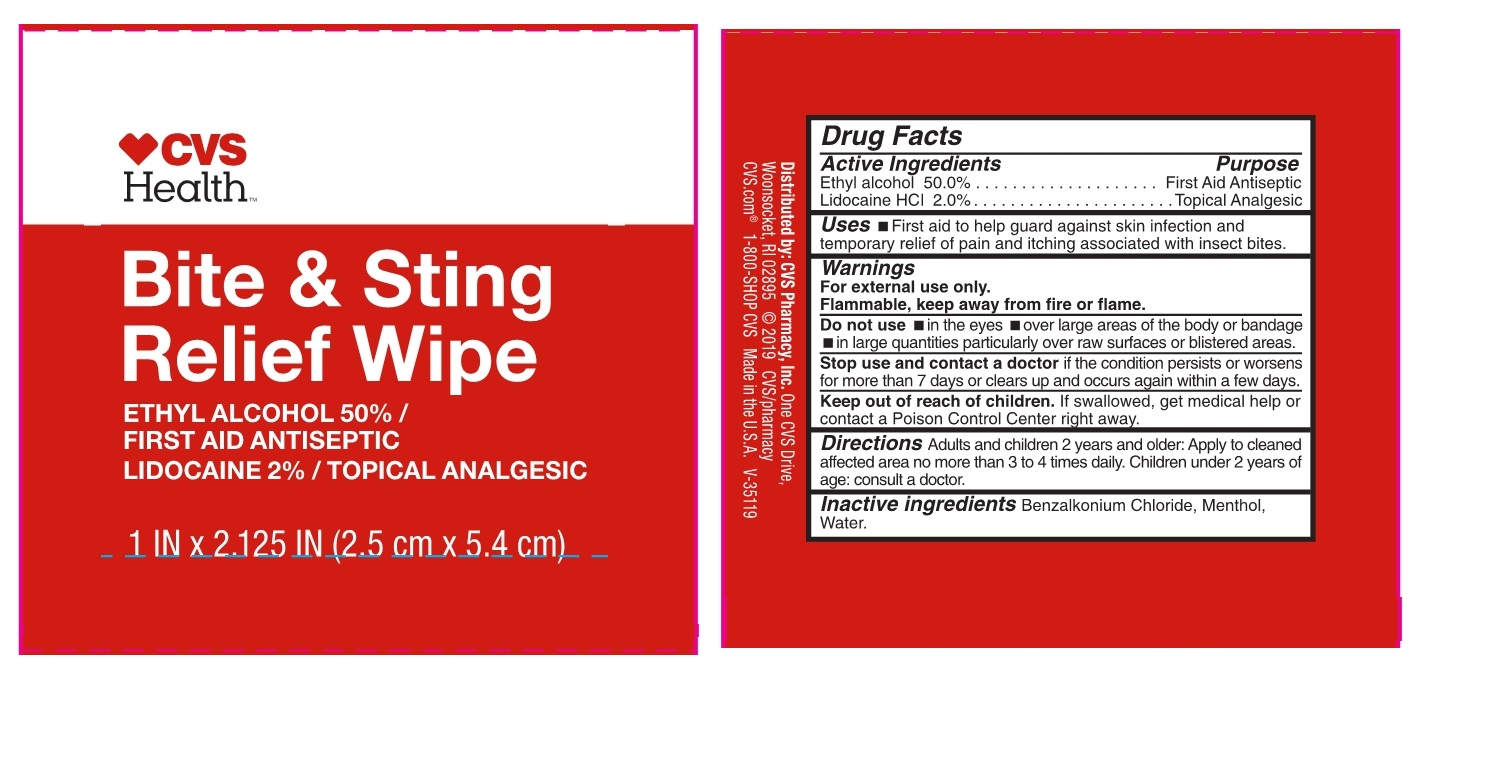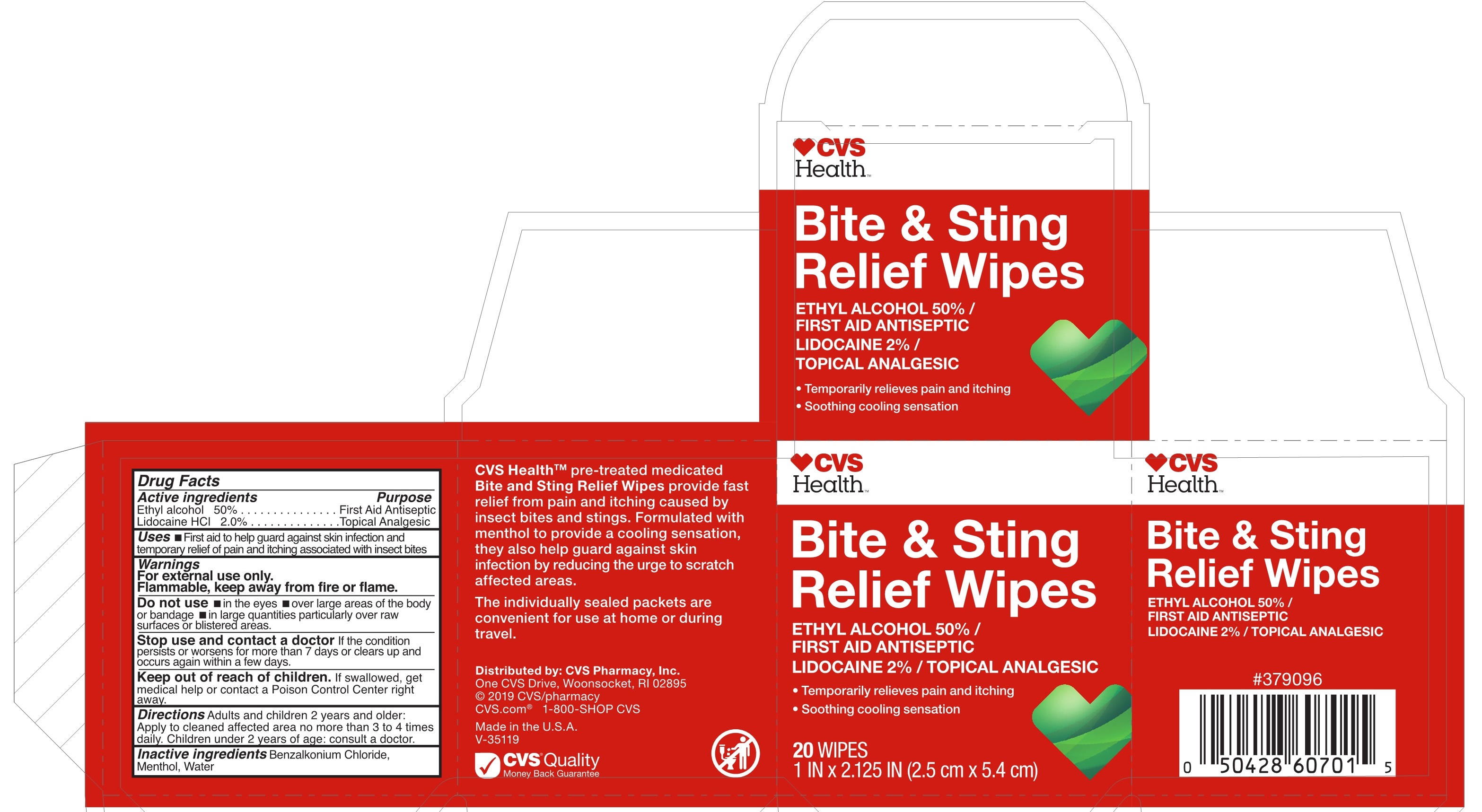 DRUG LABEL: Bite and Sting Relief Wipe
NDC: 69842-190 | Form: Cloth
Manufacturer: CVS
Category: otc | Type: HUMAN OTC DRUG LABEL
Date: 20190705

ACTIVE INGREDIENTS: ALCOHOL 50 mL/100 mL; LIDOCAINE 2 g/100 mL
INACTIVE INGREDIENTS: BENZALKONIUM CHLORIDE; MENTHOL; WATER

Active Ingredients

Ethyl Alcohol 50.0%

Lidocaine HCL 2.0%

Purpose

First Aid Antiseptic
Topical Analgesic

Uses

- First aid to help guard against skin infection and temporary relief of pain and itching assocaiated with insect bites.

Warnings

For external use only.

Flammable, keep away from fire or flame.

Do not use

- in the eyes over large areas of the body or bandage.
- in large quantities particularly over raw surfaces or blistered areas.

Stop use and contact a doctor if the condition persists or worsens for more than 7 days or clears up and occurs again within a few days.

Keep out of reach of children if swallowed, get medical help or contact a Poison Control Center right away.

Directions

Adults and children 2 years and older: Apply to clean affected area no more than 3 to 4 times daily. Children under 2 years of age: consult a doctor.

Inactive ingredients

Benzalkonium Chloride, Menthol, Water.